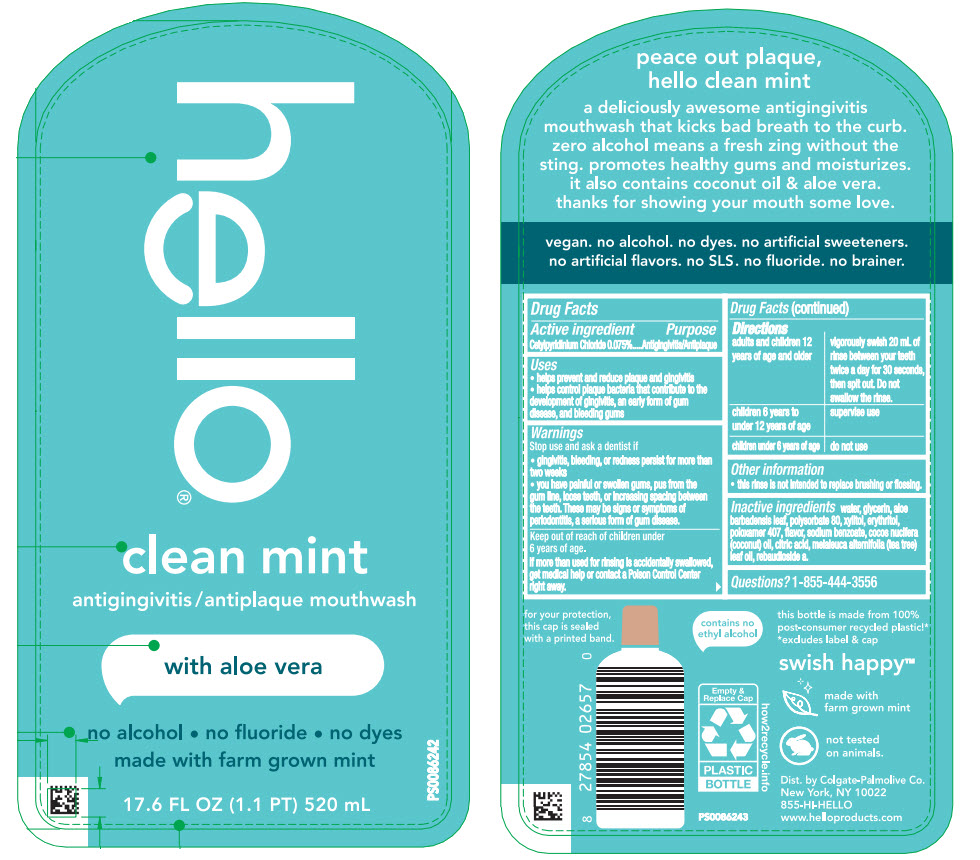 DRUG LABEL: Hello Clean Mint
NDC: 35000-510 | Form: MOUTHWASH
Manufacturer: Colgate-Palmolive Company
Category: otc | Type: HUMAN OTC DRUG LABEL
Date: 20251223

ACTIVE INGREDIENTS: CETYLPYRIDINIUM CHLORIDE 15 mg/20 mL
INACTIVE INGREDIENTS: WATER; GLYCERIN; ALOE VERA LEAF; POLYSORBATE 80; ERYTHRITOL; XYLITOL; POLOXAMER 407; COCONUT OIL; SODIUM BENZOATE; CITRIC ACID MONOHYDRATE; REBAUDIOSIDE A; TEA TREE OIL

Hello® Clean Mint
with aloe vera

Drug Facts

Active ingredient

Cetylpyridinium Chloride 0.075%

Purpose

Antigingivitis/Antiplaque

Uses

- helps prevent and reduce plaque and gingivitis
- helps control plaque bacteria that contribute to the development of gingivitis, an early form of gum disease, and bleeding gums

Warnings

Stop use and ask a dentist if

- gingivitis, bleeding, or redness persist for more than two weeks
- you have painful or swollen gums, pus from the gum line, loose teeth, or increasing spacing between the teeth. These may be signs or symptoms of periodontitis, a serious form of gum disease.

Keep out of reach of children under 6 years of age.

If more than used for rinsing is accidentally swallowed, get medical help or contact a Poison Control Center right away.

Directions

adults and children 12 years of age and older | vigorously swish 20 mL of rinse between your teeth twice a day for 30 seconds, then spit out. Do not swallow the rinse.
children 6 years to under 12 years of age | supervise use
children under 6 years of age | do not use

Other information

- this rinse is not intended to replace brushing or flossing.

Inactive ingredients

water, glycerin, aloe barbadensis leaf, polysorbate 80, xylitol, erythritol, poloxamer 407, flavor, sodium benzoate, cocos nucifera (coconut) oil, citric acid, melaleuca alternifolia (tea tree) leaf oil, rebaudioside a.

Questions?

1-855-444-3556

Dist. by Colgate-Palmolive Co.
New York, NY 10022

PRINCIPAL DISPLAY PANEL - 520 mL Bottle Label

hello®

clean mint
antigingivitis / antiplaque mouthwash

with aloe vera

no alcohol • no fluoride • no dyes
made with farm grown mint

17.6 FL OZ (1.1 PT) 520 mL

PS0086242